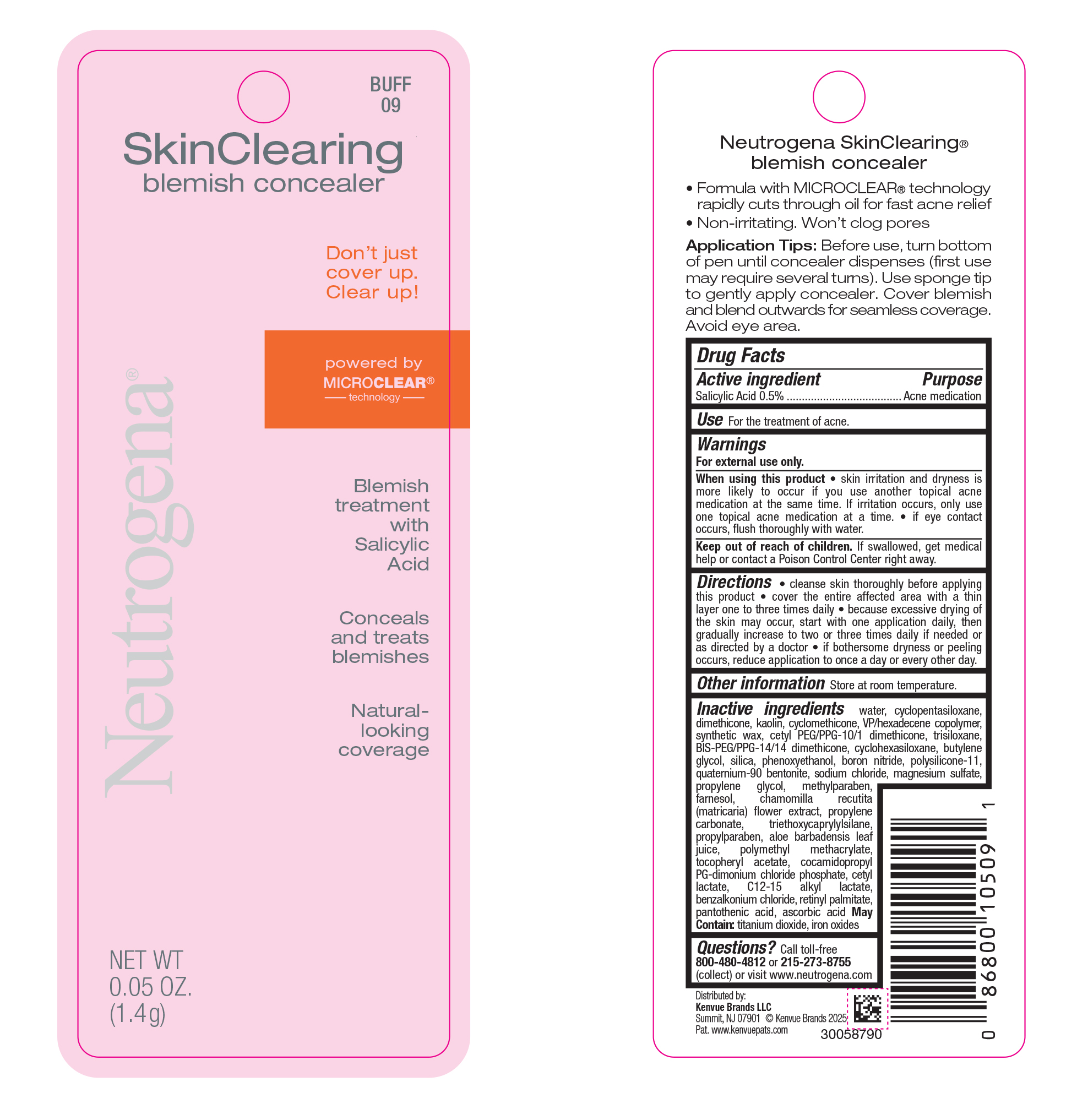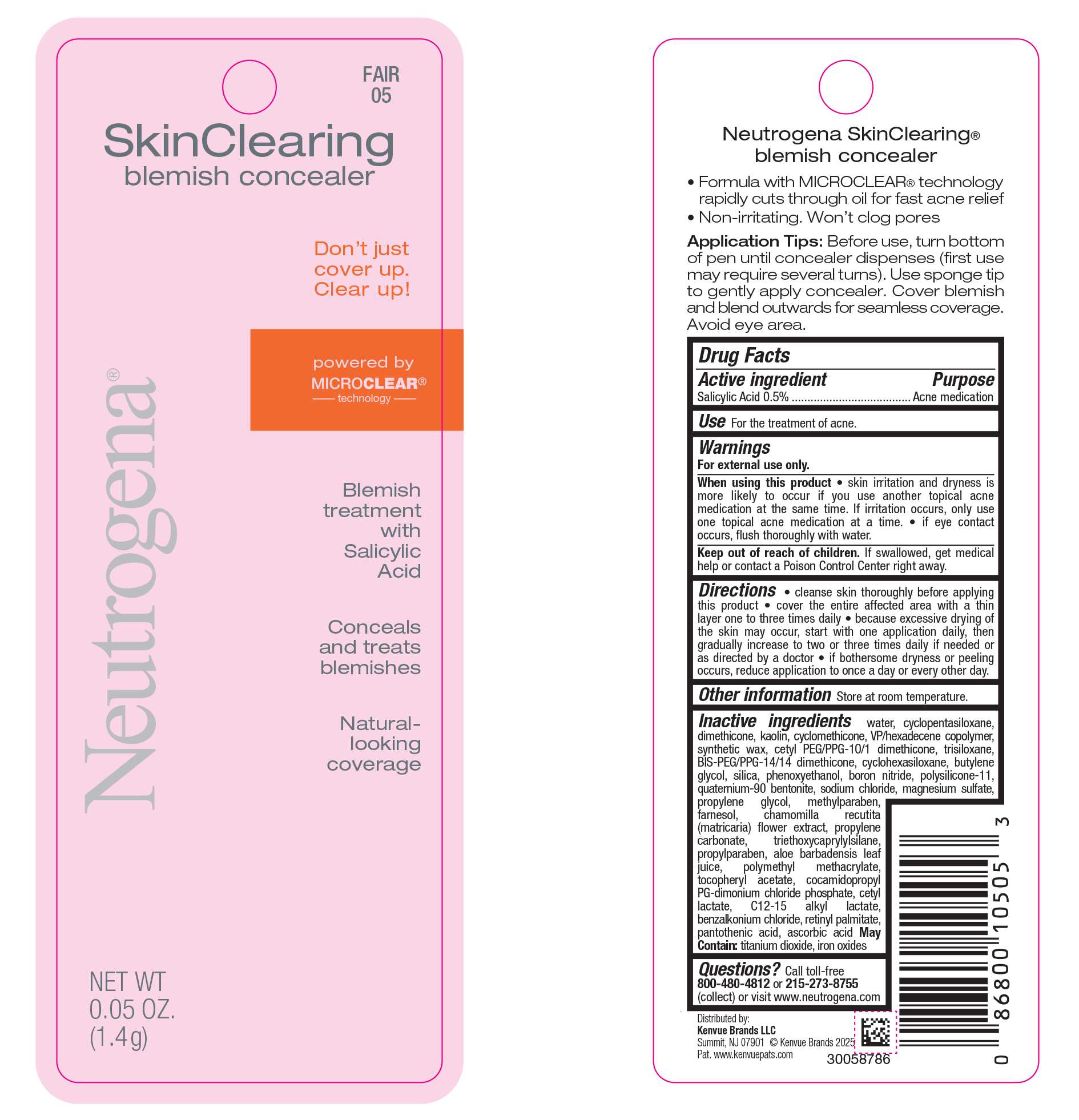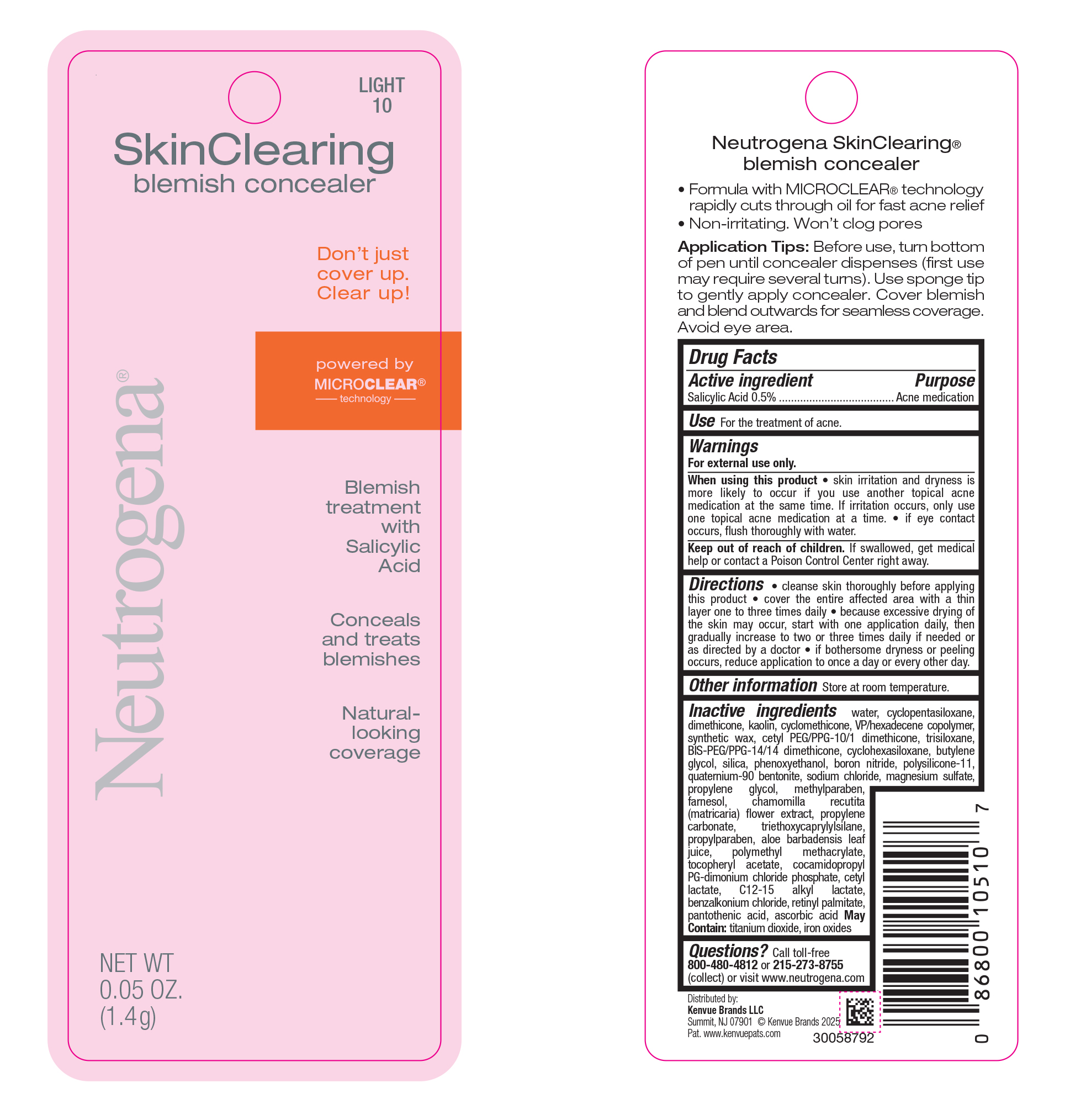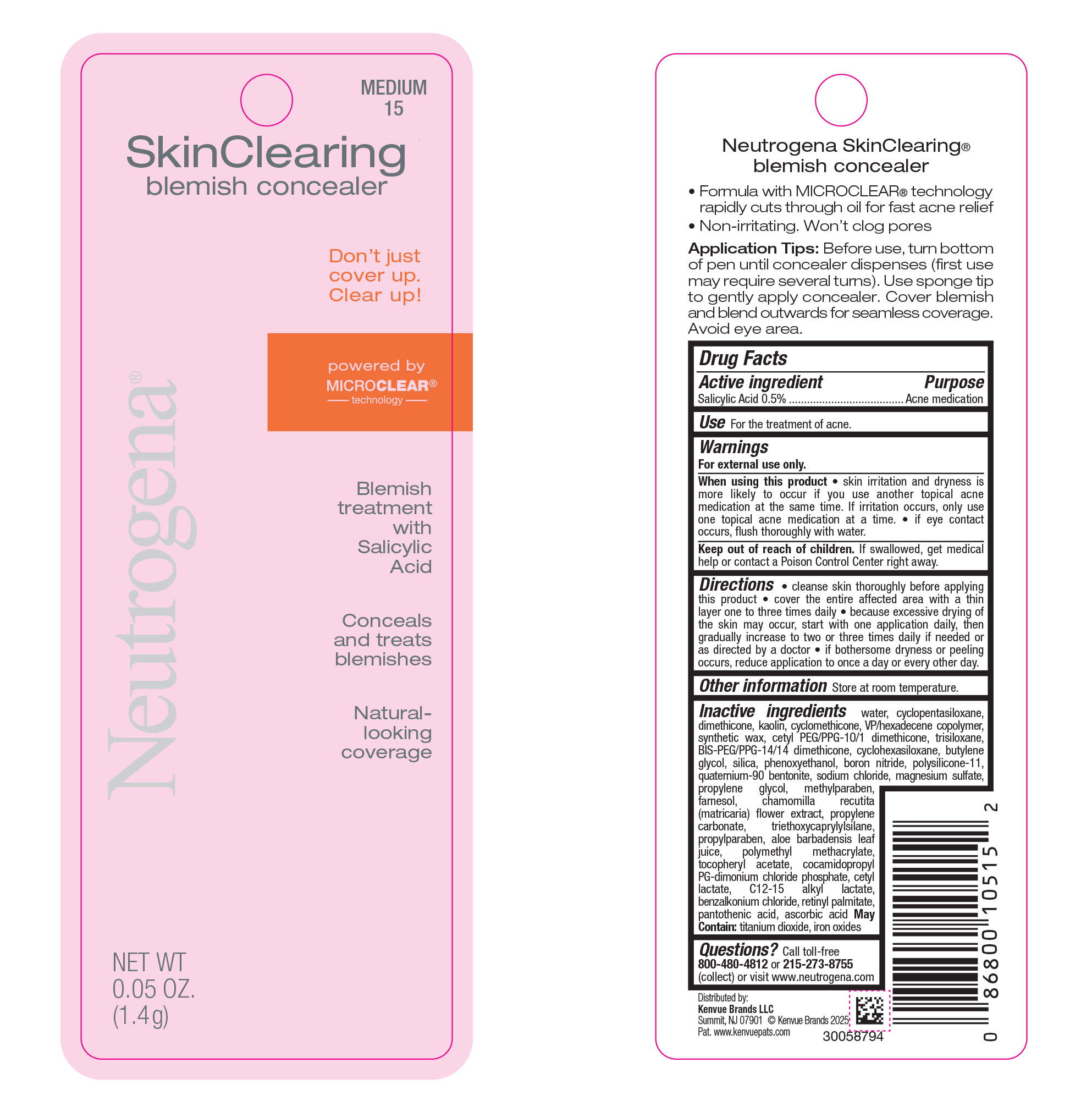 DRUG LABEL: Neutrogena Skin Clearing Blemish Concealer - Light 10
NDC: 69968-0805 | Form: CREAM
Manufacturer: Kenvue Brands LLC
Category: otc | Type: HUMAN OTC DRUG LABEL
Date: 20250117

ACTIVE INGREDIENTS: SALICYLIC ACID 5 mg/1 g
INACTIVE INGREDIENTS: WATER; VINYLPYRROLIDONE/HEXADECENE COPOLYMER; PHENOXYETHANOL; VITAMIN A PALMITATE; ASCORBIC ACID; BORON NITRIDE; ALOE VERA LEAF; TITANIUM DIOXIDE; ALPHA-TOCOPHEROL ACETATE; COCAMIDOPROPYL PG-DIMONIUM CHLORIDE PHOSPHATE; CYCLOMETHICONE 5; DIMETHICONE; CYCLOMETHICONE; POLY(METHYL METHACRYLATE; 450000 MW); CETYL LACTATE; BIS-PEG/PPG-14/14 DIMETHICONE; SILICON DIOXIDE; DIMETHICONE/VINYL DIMETHICONE CROSSPOLYMER (SOFT PARTICLE); PROPYLENE GLYCOL; METHYLPARABEN; CHAMOMILE; TRIETHOXYCAPRYLYLSILANE; C12-15 ALKYL LACTATE; FERROUS OXIDE; FARNESOL; KAOLIN; CETYL PEG/PPG-10/1 DIMETHICONE (HLB 5); BENZALKONIUM CHLORIDE; CYCLOMETHICONE 6; MAGNESIUM SULFATE, UNSPECIFIED; TRISILOXANE; SODIUM CHLORIDE; QUATERNIUM-90 BENTONITE; PROPYLENE CARBONATE; PROPYLPARABEN; PANTOTHENIC ACID; BUTYLENE GLYCOL

Neutrogena Skin Clearing Blemish Concealer - Fair 05
Neutrogena Skin Clearing Blemish Concealer - Buff 09
Neutrogena Skin Clearing Blemish Concealer - Light 10
Neutrogena Skin Clearing Blemish Concealer - Medium 15

Drug Facts

Active ingredient

Salicylic Acid 0.5%

Purpose

Acne medication

Use

For the treatment of acne.

Warnings

For external use only.

When using this product

• skin irritation and dryness is more likely to occur if you use another topical acne medication at the same time. If irritation occurs, only use one topical acne medication at a time.

• if eye contact occurs, flush thoroughly with water.

Keep out of reach of children. If swallowed, get medical help or contact a Poison Control Center right away.

Directions

• cleanse skin thoroughly before applying this product.

• cover the entire affected area with a thin layer one to three times daily

• because excessive drying of the skin may occur, start with one application daily, then gradually increase to two or three times daily if needed or as directed by a doctor

• if bothersome dryness or peeling occurs, reduce application to once a day or every other day.

Other Information

Store at room temperature.

Inactive ingredients

water, cyclopentasiloxane, dimethicone, kaolin, cyclomethicone, VP/hexadecene copolymer, synthetic Wax, cetyl PEG/PPG-10/1 dimethicone, trisiloxane, BIS-PEG/PPG-14/14 dimethicone, cyclohexasiloxane, butylene Glycol, silica, phenoxyethanol, boron nitride, polysilicone-11, quatermium-90 bentonite, sodium chloride, magnesium sulfate, propylene glycol, methylparaben, farnesol, chamomilla recutita (matricaria) flower extract, propylene carbonate, triethoxycaprylylsilane, propylparaben, aloe barbadensis leaf juice, polymethyl methacrylate, tocopheryl acetate, cocamidopropyl PG-dimoniium chloride phospate, cetyl lactate, C12-15 alkyl lactate, benzalkonium chloride, retinyl palmitate, pantothenic acid, ascorbic Acid May Contain: titanium dioxide, iron oxides

Questions?

Call toll-free 800-480-4812 or 215-273-8755 (collect) or visit www.neutrogena.com

Distributed by:

Kenvue Brands LLC
Summit, NJ 07901

PRINCIPAL DISPLAY PANEL - 1.4 g Applicator Blister Pack - Fair 05

FAIR

05

SkinClearing

blemish concealer

Don’t just

cover up.

Clear up!

powered by

MICROCLEAR®

------technology---------

Blemish

treatment

with

Salicylic

Acid

Conceals

and treats

blemishes

Natural-

looking

coverage

Neutrogena®

NET WT

0.05 OZ.

(1.4g)

PRINCIPAL DISPLAY PANEL - 1.4 g Applicator Blister Pack - Buff 09

BUFF

09

SkinClearing

blemish concealer

Don’t just

cover up.

Clear up!

powered by

MICROCLEAR®

------technology---------

Blemish

treatment

with

Salicylic

Acid

Conceals

and treats

blemishes

Natural-

looking

coverage

Neutrogena®

NET WT

0.05 OZ.

(1.4g)

PRINCIPAL DISPLAY PANEL - 1.4 g Applicator Blister Pack - Light 10

LIGHT

10

SkinClearing

blemish concealer

Don’t just

cover up.

Clear up!

powered by

MICROCLEAR®

------technology---------

Blemish

treatment

with

Salicylic

Acid

Conceals

and treats

blemishes

Natural-

looking

coverage

Neutrogena®

NET WT

0.05 OZ.

(1.4g)

PRINCIPAL DISPLAY PANEL - 1.4 g Applicator Blister Pack - Medium 15

MEDIUM

15

SkinClearing

blemish concealer

Don’t just

cover up.

Clear up!

powered by

MICROCLEAR®

------technology---------

Blemish

treatment

with

Salicylic

Acid

Conceals

and treats

blemishes

Natural-

looking

coverage

Neutrogena®

NET WT

0.05 OZ.

(1.4g)